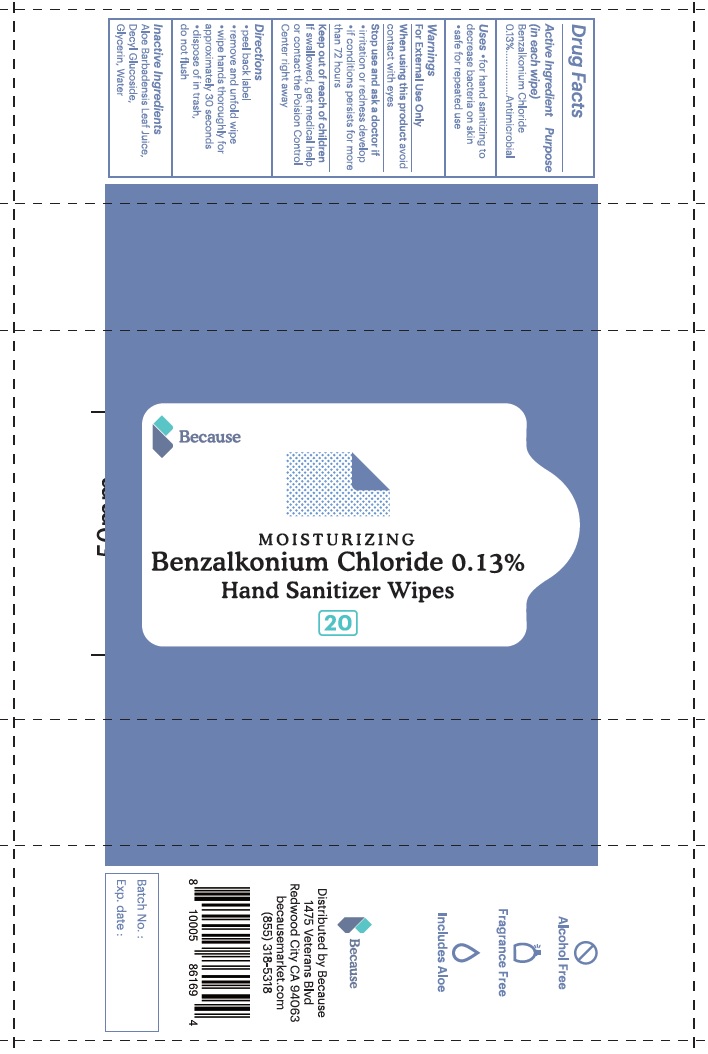 DRUG LABEL: Because
NDC: 74088-001 | Form: CLOTH
Manufacturer: PORTOFINO LABS, INC
Category: otc | Type: HUMAN OTC DRUG LABEL
Date: 20211101

ACTIVE INGREDIENTS: BENZALKONIUM CHLORIDE 1.3 mg/1 1
INACTIVE INGREDIENTS: WATER; GLYCERIN; ALOE VERA LEAF; DECYL GLUCOSIDE

Benzalkonium chloride impregnated moist hand wipes

Active lngredient

Benzalkonium chloride 0.13%

Purpose

Antimicrobial

Uses

- for hand sanitizing to decrease bacteria on skin
- safe for repeated use

Warnings

For external use only

When using this product avoid contact with eyes

Stop use and ask a doctor If
•irritation or redness develop
•if conditions persists for more than 72 hours

Keep out of reach of children
If swallowed, get medical help or contact the Poision Control Center right away

Directions

- peel back label
- remove and unfold wipe
- wipe hands thoroughly for approximately 30 seconds
- dispose of in trash
- do not flush

Inactive Ingredients

Aloe barbadensis Leaf Juice, Decyl Glucoside, Glycerin, Water